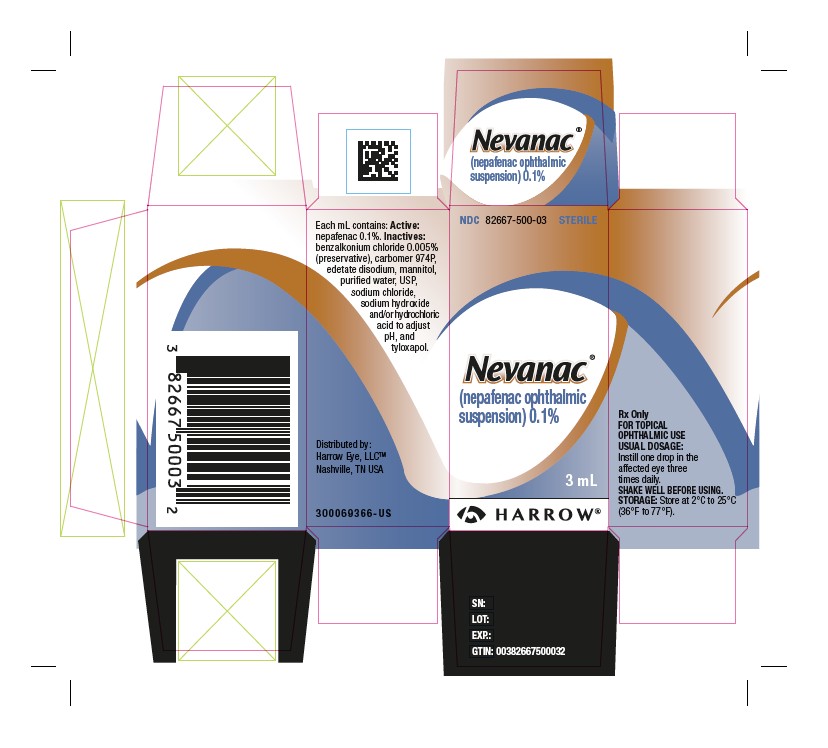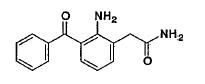 DRUG LABEL: NEVANAC
NDC: 82667-500 | Form: SUSPENSION/ DROPS
Manufacturer: Harrow Eye, LLC
Category: prescription | Type: HUMAN PRESCRIPTION DRUG LABEL
Date: 20241105

ACTIVE INGREDIENTS: NEPAFENAC 1 mg/1 mL
INACTIVE INGREDIENTS: BENZALKONIUM CHLORIDE; MANNITOL; CARBOMER HOMOPOLYMER TYPE B (ALLYL PENTAERYTHRITOL CROSSLINKED); SODIUM CHLORIDE; TYLOXAPOL; EDETATE DISODIUM; SODIUM HYDROXIDE; HYDROCHLORIC ACID; WATER

HIGHLIGHTS OF PRESCRIBING INFORMATION

These highlights do not include all the information needed to use NEVANAC safely and effectively. See full prescribing information for NEVANAC.
NEVANAC®(nepafenac ophthalmic suspension) 0.1%, for topical ophthalmic use
Initial U.S. Approval: 2005

1 INDICATIONS AND USAGE

NEVANAC is a nonsteroidal, anti-inflammatory prodrug indicated for the treatment of pain and inflammation associated with cataract surgery. (1)

2 DOSAGE AND ADMINISTRATION

One drop of NEVANAC should be applied to the affected eye three times daily beginning 1 day prior to cataract surgery, continued on the day of surgery and through the first 2 weeks of the postoperative period. (2.1)

3 DOSAGE FORMS AND STRENGTHS

Sterile ophthalmic suspension 0.1%

3 mL in a 4 mL bottle (3)

4 CONTRAINDICATIONS

Hypersensitivity to any of the ingredients in the formula or to other non-steroidal anti-inflammatory drugs (NSAIDS). (4)

5 WARNINGS AND PRECAUTIONS

- Increased bleeding time due to interference with thrombocyte aggregation (5.1)
- Delayed Healing (5.2)
- Corneal effects, including keratitis (5.3)

6 ADVERSE REACTIONS

Most common adverse reactions (5% to 10%) are capsular opacity, decreased visual acuity, foreign body sensation, increased intraocular pressure (IOP), and sticky sensation. (6.1)

To report SUSPECTED ADVERSE REACTIONS, contact Harrow Eye, LLC at 833-4HARROW(427769) or FDA at 1-800-FDA-1088 or www.fda.gov/medwatch.

FULL PRESCRIBING INFORMATION

1 INDICATIONS AND USAGE

NEVANAC® 0.1% is indicated for the treatment of pain and inflammation associated with cataract surgery.

2 DOSAGE AND ADMINISTRATION

2.1 Recommended Dosing

One drop of NEVANAC 0.1% should be applied to the affected eye three times daily beginning 1 day prior to cataract surgery, continued on the day of surgery and through the first 2 weeks of the postoperative period. Shake the container well prior to dosing.

2.2 Use With Other Topical Ophthalmic Medications

NEVANAC 0.1% may be administered in conjunction with other topical ophthalmic medications, such as beta-blockers, carbonic anhydrase inhibitors, alpha-agonists, cycloplegics, and mydriatics.

If more than one topical ophthalmic medication is being used, the medicines must be administered at least 5 minutes apart.

3 DOSAGE FORMS AND STRENGTHS

Sterile ophthalmic suspension 0.1%

3 mL in a 4 mL bottle

4 CONTRAINDICATIONS

NEVANAC 0.1% is contraindicated in patients with previously demonstrated hypersensitivity to any of the ingredients in the formula or to other non-steroidal anti-inflammatory drugs (NSAIDs).

5 WARNINGS AND PRECAUTIONS

5.1 Increased Bleeding Time

With some NSAIDs, including NEVANAC 0.1%, there exists the potential for increased bleeding time due to interference with thrombocyte aggregation. There have been reports that ocularly applied NSAIDs may cause increased bleeding of ocular tissues (including hyphema) in conjunction with ocular surgery.

It is recommended that NEVANAC 0.1% be used with caution in patients with known bleeding tendencies, or who are receiving other medications, which may prolong bleeding time.

5.2 Delayed Healing

Topical NSAIDs, including NEVANAC 0.1%, may slow or delay healing. Topical corticosteroids are also known to slow or delay healing. Concomitant use of topical NSAIDs and topical steroids may increase the potential for healing problems.

5.3 Corneal Effects

Use of topical NSAIDs may result in keratitis. In some susceptible patients, continued use of topical NSAIDs may result in epithelial breakdown, corneal thinning, corneal erosion, corneal ulceration, or corneal perforation. These events may be sight threatening. Patients with evidence of corneal epithelial breakdown should immediately discontinue use of topical NSAIDs, including NEVANAC 0.1%, and should be closely monitored for corneal health.

Postmarketing experience with topical NSAIDs suggests that patients with complicated ocular surgeries, corneal denervation, corneal epithelial defects, diabetes mellitus, ocular surface diseases (e.g., dry eye syndrome), rheumatoid arthritis, or repeat ocular surgeries within a short period of time may be at increased risk for corneal adverse events, which may become sight threatening. Topical NSAIDs should be used with caution in these patients.

Postmarketing experience with topical NSAIDs also suggests that use more than 1 day prior to surgery or use beyond 14 days post-surgery may increase patient risk and severity of corneal adverse events.

5.4 Contact Lens Wear

NEVANAC®0.1% should not be administered while using contact lenses.

6 ADVERSE REACTIONS

The following adverse reactions are discussed in greater detail in other sections of labeling:

- Increased Bleeding Time [see Warnings and Precautions (5.1)]
- Delayed Healing [see Warnings and Precautions (5.2)]
- Corneal Effects [see Warnings and Precautions (5.3)]

6.1 Clinical Trials Experience

Because clinical trials are conducted under widely varying conditions, adverse reaction rates observed in the clinical trials of a drug cannot be directly compared to the rates in the clinical trials of another drug and may not reflect the rates observed in practice.

The most frequently reported ocular adverse reactions following cataract surgery were capsular opacity, decreased visual acuity, foreign body sensation, increased intraocular pressure (IOP), and sticky sensation. These reactions occurred in approximately 5% to 10% of patients.

Other ocular adverse reactions occurring at an incidence of approximately 1% to 5% included conjunctival edema, corneal edema, dry eye, lid margin crusting, ocular discomfort, ocular hyperemia, ocular pain, ocular pruritus, photophobia, tearing, and vitreous detachment.

Some of these reactions may be the consequence of the cataract surgical procedure.

Non-ocular adverse reactions reported at an incidence of 1% to 4% included headache, hypertension, nausea/vomiting, and sinusitis.

8 USE IN SPECIFIC POPULATIONS

8.1 Pregnancy

Teratogenic Effects

Pregnancy Category C:Reproduction studies performed with nepafenac in rabbits and rats at oral doses up to 10 mg/kg/day have revealed no evidence of teratogenicity due to nepafenac, despite the induction of maternal toxicity. At this dose, the animal plasma exposure to nepafenac and amfenac was approximately 260 and 2400 times human plasma exposure at the recommended human topical ophthalmic dose for rats and 80 and 680 times human plasma exposure for rabbits, respectively. In rats, maternally toxic doses greater than or equal to 10 mg/kg were associated with dystocia, increased post-implantation loss, reduced fetal weights and growth, and reduced fetal survival.

Nepafenac has been shown to cross the placental barrier in rats. There are no adequate and well-controlled studies in pregnant women. Because animal reproduction studies are not always predictive of human response, NEVANAC 0.1% should be used during pregnancy only if the potential benefit justifies the potential risk to the fetus.

Non-Teratogenic Effects

Because of the known effects of prostaglandin biosynthesis inhibiting drugs on the fetal cardiovascular system (closure of the ductus arteriosus), the use of NEVANAC 0.1% during late pregnancy should be avoided.

8.3 Nursing Mothers

Nepafenac is excreted in the milk of lactating rats. It is not known whether this drug is excreted in human milk. Because many drugs are excreted in human milk, caution should be exercised when NEVANAC 0.1% ophthalmic suspension is administered to a nursing woman.

8.4 Pediatric Use

The safety and effectiveness of NEVANAC 0.1% in pediatric patients below the age of 10 years have not been established.

8.5 Geriatric Use

No overall differences in safety and effectiveness have been observed between elderly and younger patients.

11 DESCRIPTION

NEVANAC®0.1% is a sterile, topical NSAID prodrug for ophthalmic use. Each mL of NEVANAC 0.1% contains 3 mg of nepafenac. Nepafenac is designated chemically as 2-amino-3-benzoylbenzeneacetamide with an empirical formula of C15H14N2O2. The structural formula of nepafenac is:

Nepafenac is a yellow crystalline powder. The molecular weight of nepafenac is 254.28 g/mol. NEVANAC, 0.1% is supplied as a sterile, aqueous suspension with a pH approximately of 7.4.

The osmolality of NEVANAC 0.1% is approximately 305 mOsm/kg.

Each mL of NEVANAC 0.1% contains: Active:nepafenac 0.1%. Inactives:benzalkonium chloride 0.005% (preservative), carbomer 974P, edetate disodium, mannitol, purified water, USP, sodium chloride, sodium hydroxide and/or hydrochloric acid to adjust pH, and tyloxapol.

12 CLINICAL PHARMACOLOGY

12.1 Mechanism of Action

After topical ocular dosing, nepafenac penetrates the cornea and is converted by ocular tissue hydrolases to amfenac, an NSAID. Amfenac is thought to inhibit the action of prostaglandin H synthase (cyclooxygenase), an enzyme required for prostaglandin production.

12.3 Pharmacokinetics

Low but quantifiable plasma concentrations of nepafenac and amfenac were observed in the majority of subjects 2 and 3 hours post dose, respectively, following bilateral topical ocular 3 times-daily dosing of nepafenac ophthalmic suspension, 0.1%. The mean steady-state Cmaxfor nepafenac and for amfenac were 0.310 ± 0.104 ng/mL and 0.422 ± 0.121 ng/mL, respectively, following ocular administration.

Nepafenac at concentrations up to 300 ng/mL did not inhibit the in vitrometabolism of 6 specific marker substrates of cytochrome P450 (CYP) isozymes (CYP1A2, CYP2C9, CYP2C19, CYP2D6, CYP2E1, and CYP3A4). Therefore, drug-drug interactions involving CYP-mediated metabolism of concomitantly administered drugs are unlikely. Drug-drug interactions mediated by protein binding are also unlikely.

13 NONCLINICAL TOXICOLOGY

13.1 Carcinogenesis, Mutagenesis, Impairment of Fertility

Nepafenac has not been evaluated in long-term carcinogenicity studies. Increased chromosomal aberrations were observed in Chinese hamster ovary cells exposed in vitroto nepafenac suspension. Nepafenac was not mutagenic in the Ames assay or in the mouse lymphoma forward mutation assay. Oral doses up to 5,000 mg/kg did not result in an increase in the formation of micronucleated polychromatic erythrocytes in vivoin the mouse micronucleus assay in the bone marrow of mice.

Nepafenac did not impair fertility when administered orally to male and female rats at 3 mg/kg (approximately 90 and 380 times the plasma exposure to the parent drug, nepafenac, and the active metabolite, amfenac, respectively, at the recommended human topical ophthalmic dose).

14 CLINICAL STUDIES

In two double-masked, randomized clinical trials in which patients were dosed 3 times daily beginning 1 day prior to cataract surgery, continued on the day of surgery and for the first 2 weeks of the postoperative period, NEVANAC 0.1% demonstrated superior clinical efficacy compared to its vehicle in treating postoperative pain and inflammation.

Patients treated with NEVANAC®0.1% were less likely to have ocular pain and measurable signs of inflammation (cells and flare) in the early postoperative period through the end of treatment than those treated with its vehicle.

For ocular pain in both studies, a significantly higher percentage of patients (approximately 80%) in the nepafenac group reported no ocular pain on the day following cataract surgery (Day 1) compared to those in the vehicle group (approximately 50%).

Results from clinical studies indicated that NEVANAC 0.1% has no significant effect upon IOP; however, changes in IOP may occur following cataract surgery.

16 HOW SUPPLIED/STORAGE AND HANDLING

NEVANAC®0.1% is supplied in a white, oval, low density polyethylene dispenser with a natural low density polyethylene dispensing plug and gray polypropylene cap. The 1.7 mL fill is presented in an overwrap, which provides tamper evidence to the package. Tamper evidence for the 3 mL fill is provided with a shrink band around the closure and neck area of the package.

3 mL in a 4 mL bottle……………………………………………………………………………NDC 82667-500-03

Storage:Store at 2°C to 25°C (36°F to 77°F).

17 PATIENT COUNSELING INFORMATION

Slow or Delayed Healing

Advise the patient of the possibility that slow or delayed healing may occur while using NSAIDs [see Warnings and Precautions (5.2)] .

Avoiding Contamination of the Product

Advise the patient to avoid allowing the tip of the dispensing container to contact the eye or surrounding structures because this could cause the tip to become contaminated by common bacteria known to cause ocular infections. Serious damage to the eye and subsequent loss of vision may result from using contaminated solutions.

Use of the same bottle for both eyes is not recommended with topical eye drops that are used in association with surgery.

Contact Lens Wear

Advise the patient that NEVANAC 0.1% should not be administered while wearing contact lens [see Warnings and Precautions (5.4)] .

Intercurrent Ocular Conditions

Advise the patient that if they develop an intercurrent ocular condition (e.g., trauma, or infection) or have ocular surgery, they should immediately seek their physician’s advice concerning the continued use of the multi-dose container [see Warnings and Precautions (5.1)] .

Concomitant Topical Ocular Therapy

If more than one topical ophthalmic medication is being used, the medicines must be administered at least 5 minutes apart [see Dosage and Administration (2.2)] .

Shake Well Before Use

Advise the patient to shake the container well [see Dosage and Administration (2.1)] .

Distributed by:
Harrow Eye, LLC ™
Nashville, TN USA

PRINCIPAL DISPLAY PANEL

NDC 82667-500-03
STERILE

Nevanac®
(nepafenac ophthalmic
suspension) 0.1%
3 mL
HARROW®